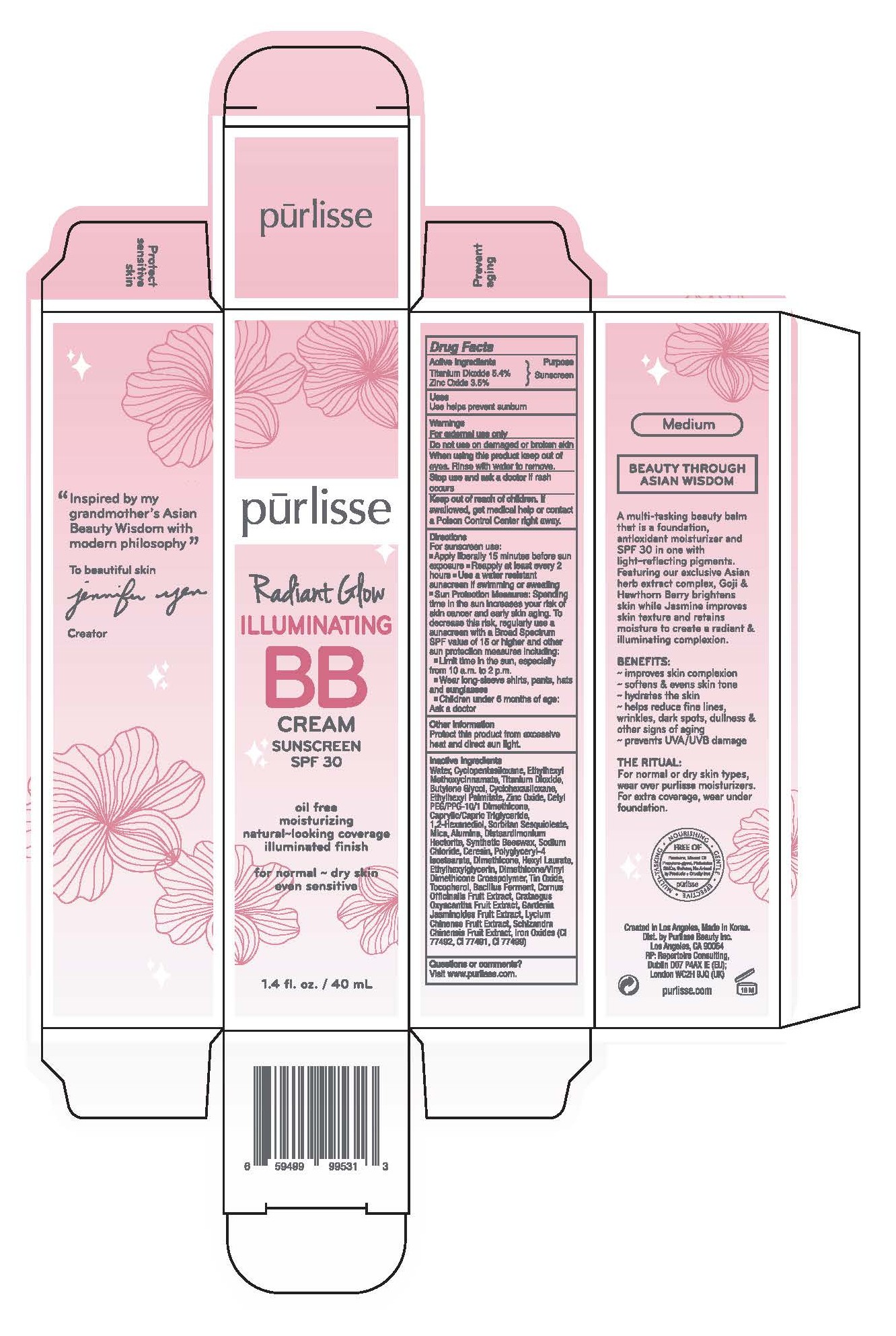 DRUG LABEL: Radiant Glow Illuminating BB Cream Sunscreen SPF 30 - Medium
NDC: 72407-438 | Form: CREAM
Manufacturer: Pur-lisse Beauty, LLC
Category: otc | Type: HUMAN OTC DRUG LABEL
Date: 20251231

ACTIVE INGREDIENTS: ZINC OXIDE 3.5 g/100 mL; OCTINOXATE 6.5 g/100 mL; TITANIUM DIOXIDE 6.35 g/100 mL
INACTIVE INGREDIENTS: SCHISANDRA CHINENSIS FRUIT; 1,2-HEXANEDIOL; ALUMINA; POLYGLYCERYL-4 ISOSTEARATE; CYCLOHEXASILOXANE; CERESIN; FERROUS OXIDE; TOCOPHEROL; DIMETHICONE/VINYL DIMETHICONE CROSSPOLYMER (SOFT PARTICLE); WATER; CRATAEGUS LAEVIGATA FRUIT; CAPRYLIC/CAPRIC TRIGLYCERIDE; HEXYL LAURATE; DIMETHICONE; SODIUM CHLORIDE; TIN OXIDE; LYCIUM CHINENSE FRUIT; ETHYLHEXYLGLYCERIN; GARDENIA JASMINOIDES FRUIT; SYNTHETIC BEESWAX; CORNUS OFFICINALIS FRUIT; CYCLOPENTASILOXANE; DISTEARDIMONIUM HECTORITE; CETYL PEG/PPG-10/1 DIMETHICONE (HLB 2); MICA; BUTYLENE GLYCOL; SORBITAN SESQUIOLEATE; ETHYLHEXYL PALMITATE; BACILLUS POLYFERMENTICUS

Drug Facts

Active Ingredients

Octinoxate 6.5%

Titanium Dioxide 6.35%

Zinc Oxide 3.5%

Purpose

Sunscreen

Uses

Use helps prevent sunburn

Warnings

For external use only

Do not use on damage or broken skin

When using this product keep out of eyes. Rinse with water to remove.

Stop use and ask a doctor if rash occurs

Keep out of reach of children. If swallowed, get medical help or contact a Poison Control Center right away.

Directions

For sunscreen use:

- Apply liberally 15 minutes before sun exposure
- Reapply at least every 2 hours
- Use a water resistant sunscreen if swimming or sweating
- Sun Protection Measures: Spending time in the sun increases your risk of skin cancer and early skin aging. To decrease this risk, regularly use a sunscreen with a Broad Spectrum SPF value of 15 or higher and other sun protection measures including:
- Limit time in the sun, especially from 10 a.m. to 2 p.m.
- Wear long-sleeve shirts, pants, hats and sunglasses
- Children under 6 months of age: Ask a doctor

Other Information

Protect this product from excessive heat and direct sun light.

Inactive Ingredients

Water, Cyclopentasiloxane, Butylene Glycol, Cyclohexasiloxane, Ethylhexyl Palmitate, Cetyl PEG/PPG-10/1 Dimethicone, Caprylic/Capric Triglyceride, 1,2-Hexanediol, Sorbitan Sesquioleate, Mica, Alumina, Disteardimonium Hectorite, Synthetic Beeswax, Sodium Chloride, Ceresin, Dimethicone, Polyglyceryl-4 Isostearate, Hexyl Laurate, Ethylhexylglycerin, Dimethicone/Vinyl Dimethicone Crosspolymer, Tin Oxide, Tocopherol, Schisandra Chinensis Fruit Extract, Lycium Chinense Fruit Extract, Cornus Officinalis Fruit Extract, Crataegus Oxyacantha Fruit Extract, Bacillus Ferment, Gardenia Jasminoides Fruit Extract, Iron Oxides (CI 77492, CI 77491, CI 77499)

Questions or comments?

Visit www.purlisse.com.

Principal Display Panel – Radiant Glow Illuminating BB Cream Sunscreen SPF 30 - Medium

pūrlisse

Radiant Glow

ILLUMINATING

BB

CREAM

SUNSCREEN

SPF 30

oil free

moisturizing

natural-looking coverage

illuminated finish

for normal – dry skin

even sensitive

1.4 fl. oz. / 40 mL